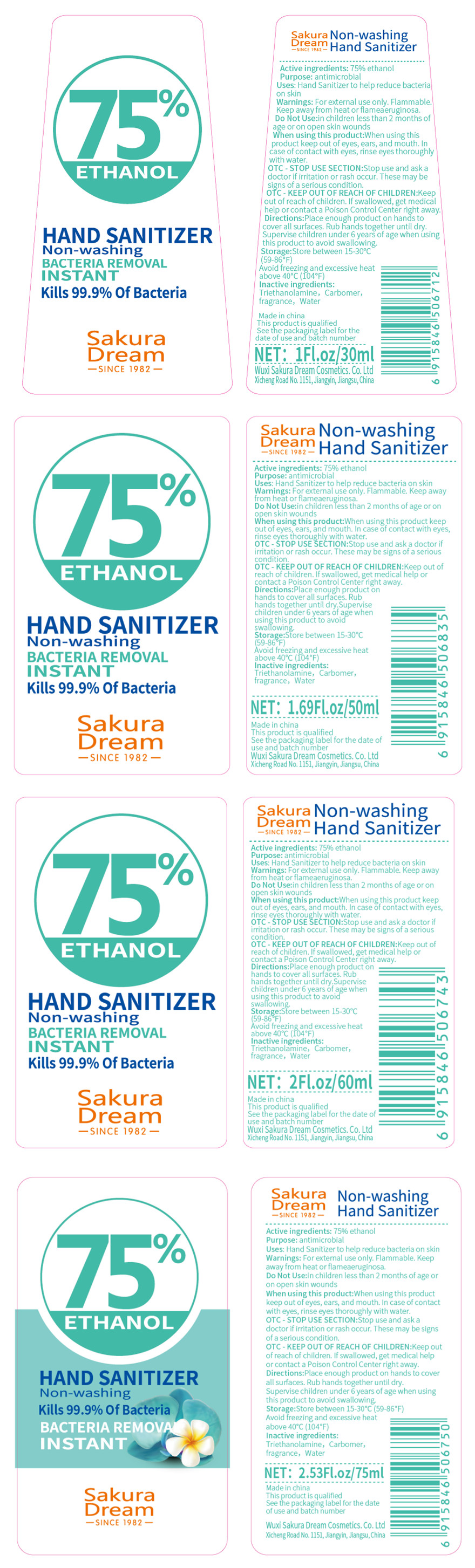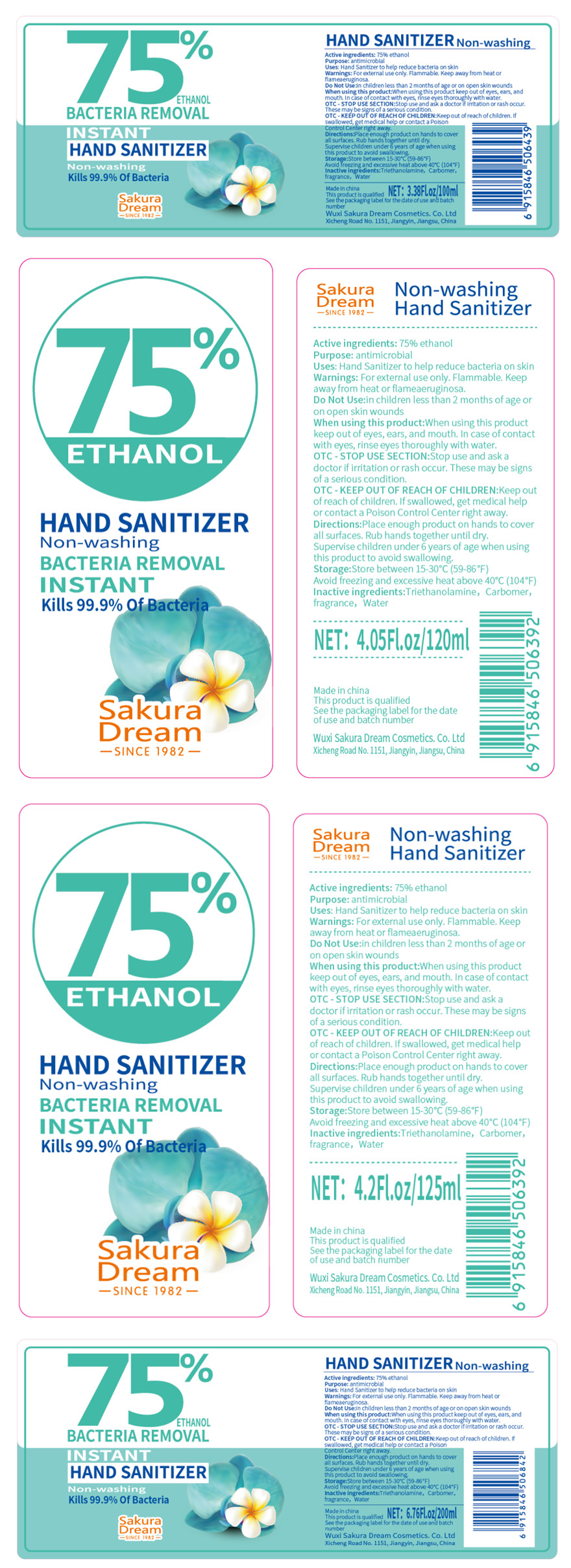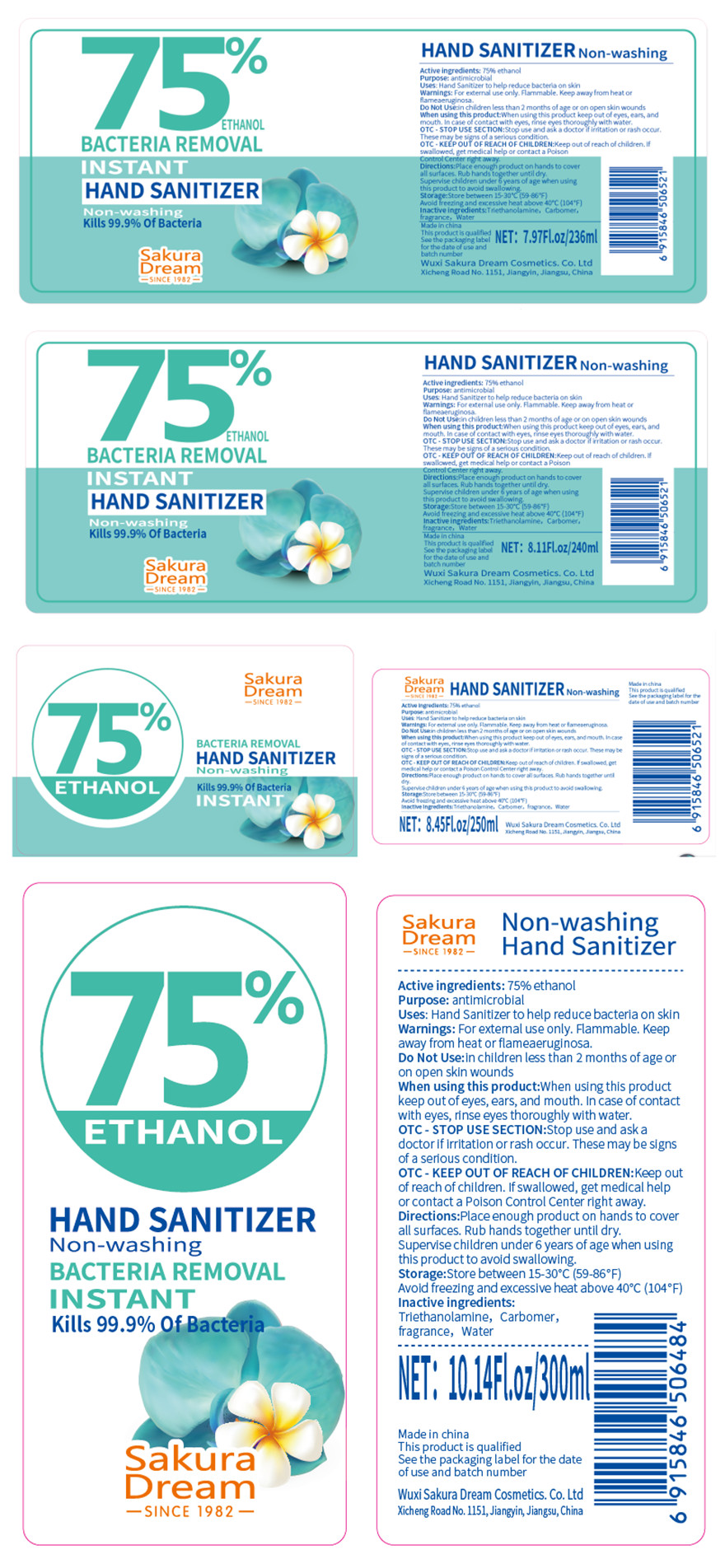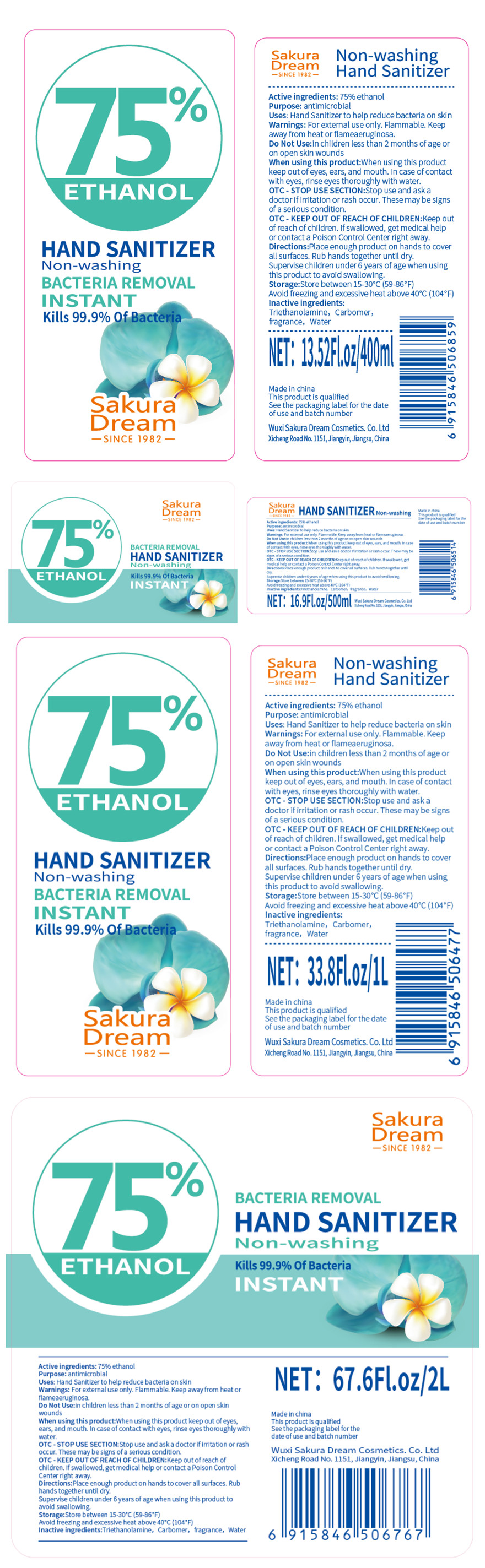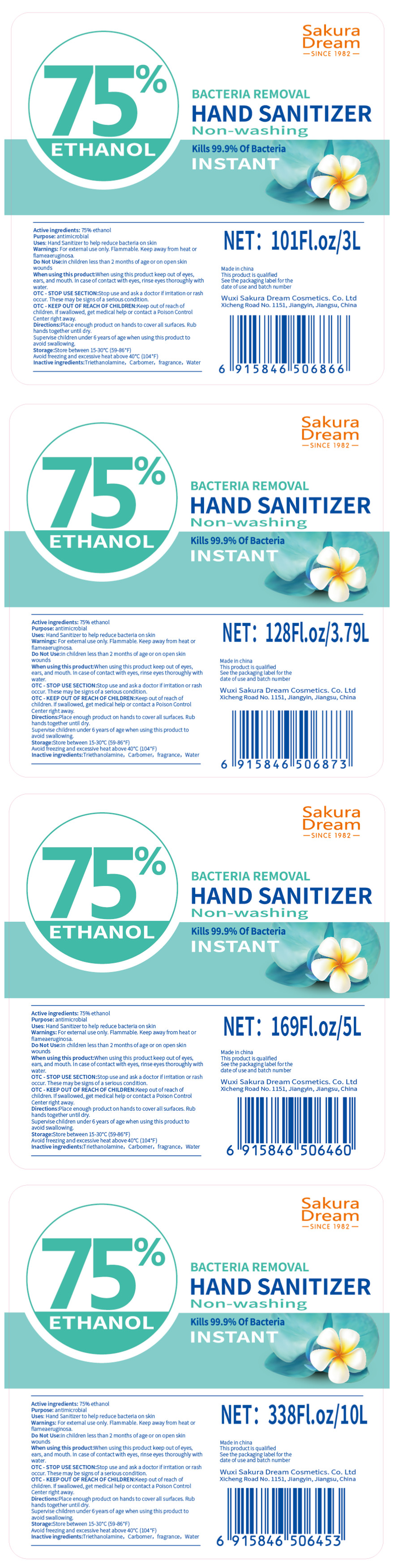 DRUG LABEL: No-washing Hand Sanitizer
NDC: 79591-001 | Form: GEL
Manufacturer: Wuxi Sakura Dream Cosmetics Co.,Ltd
Category: otc | Type: HUMAN OTC DRUG LABEL
Date: 20200711

ACTIVE INGREDIENTS: ALCOHOL 75 mL/100 mL
INACTIVE INGREDIENTS: TROLAMINE; CARBOMER HOMOPOLYMER, UNSPECIFIED TYPE; WATER

No-washing Hand Sanitizer

Active ingredients

75% ethanol

Purpose

antimicrobial

Uses

Hand Sanitizer to help reduce bacteria on skin

Warnings

For external use only.Flammable.Keep away from heat or flameaeruginosa.

Do Not Use

in children less than 2 months of age or on open skin wounds

When using this product keep out of eyes,ears,and mouth.In case of contact with eyes,rinse eyes thoroughly with water.

Stop use and ask a doctor

if irritation or rash occur.These may be signs of a serious condition.

Keep out of reach of children

If swallowed,get medical help or contact a Poison Control Center right away.

Directions

Place enough product on hands to cover all surfaces.Rub hands together until dry.Supervise children under 6 years of age

when using this product to avoid swallowing.

Other information

Store between15-30℃(59-86°F)

Avoid freezing and excessive heat above 40℃(104°F)

Inactive ingredients

Triethanolamine,Carbomer,fragrance, Water.